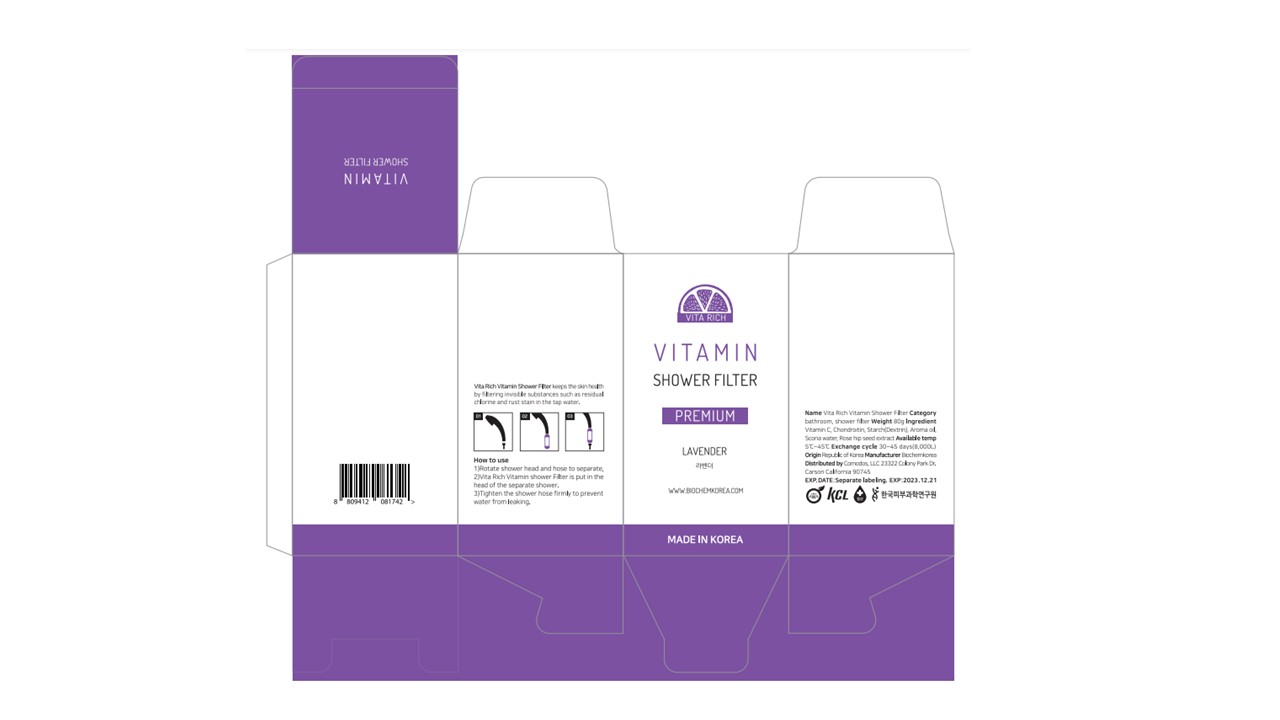 DRUG LABEL: VITA RICH
NDC: 74085-0020 | Form: LIQUID
Manufacturer: BIOCHEM KOREA CO LTD
Category: otc | Type: HUMAN OTC DRUG LABEL
Date: 20210107

ACTIVE INGREDIENTS: ASCORBIC ACID 15 g/100 g
INACTIVE INGREDIENTS: ROSA CANINA SEED; SODIUM CHONDROITIN SULFATE (PORCINE; 5500 MW)

VITA RICH VITAMIN SHOWER FILTER

Dosage Form: Liquid

Administration: Topical

WARNINGS

For external use only

Indications:

Vitamin C (ascorbic acid) is one of the most potent water-soluble antioxidants. VITA RICH shower filter reduces oxidants from the water and thus protects the skin against oxidative damage.

How to install and use the VITA RICH shower filter:

Rotate the showerhead and hose to separate.

Install the VITA RICH shower filter to the showerhead.

Connect the shower filter to the showerhead and hose and tighten.

Keep out of reach of children

Active Ingredient

Ascorbic acid (vitamin C)

PURPOSE

VITA RICH Vitamin Shower Filter reduced the concentration of the harmful oxidant in water.

Inactive Ingredients

SODIUM CHONDROITIN SULFATE

ROSA CANINA SEED